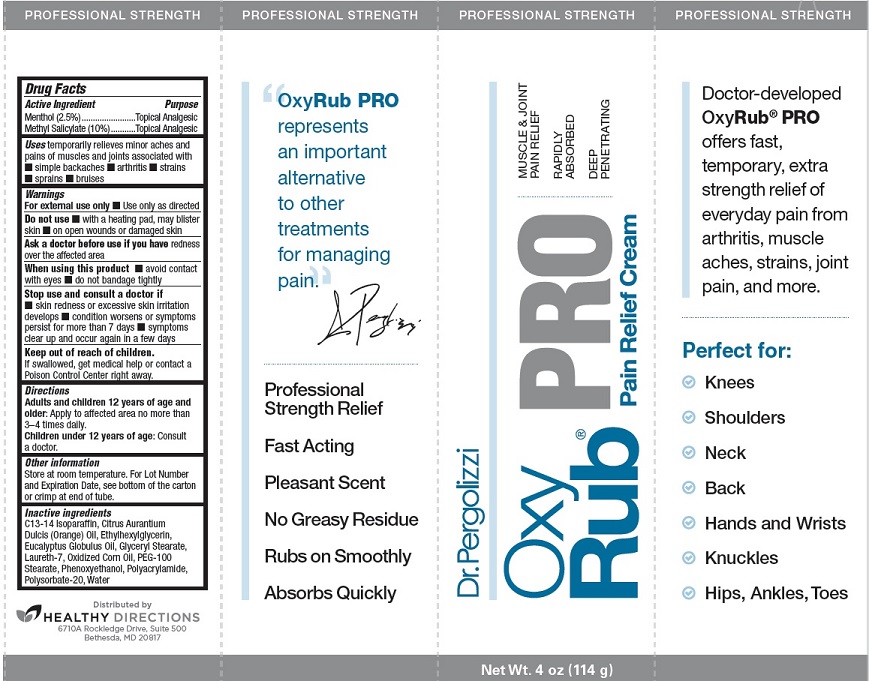 DRUG LABEL: OxyRub Pro Pain Relief
NDC: 70015-655 | Form: CREAM
Manufacturer: Healthy Directions, LLC
Category: otc | Type: HUMAN OTC DRUG LABEL
Date: 20170815

ACTIVE INGREDIENTS: MENTHOL 25.0 mg/1 g; METHYL SALICYLATE 100.0 mg/1 g
INACTIVE INGREDIENTS: ORANGE OIL; ETHYLHEXYLGLYCERIN; EUCALYPTUS OIL; GLYCERYL MONOSTEARATE; LAURETH-7; CORN OIL; PEG-100 STEARATE; PHENOXYETHANOL; POLYACRYLAMIDE (CROSSLINKED; 0.01-0.2 MOLE PERCENT BISACRYLAMIDE); POLYSORBATE 20; WATER; C13-14 ISOPARAFFIN

OxyRub PRO Pain Relief Cream, 4oz

Drug Facts

Active Ingredients

Menthol (2.5%)

Methyl Salicylate (10%)

Purpose

Topical Analgesic

Uses

Temporarily relieves minor aches and pains of muscles and joints associated with:

- simple backaches
- arthritis
- strains
- sprains
- bruises

Warnings

For external use only:Use only as directed

Do not use

- with a heating pad, may blister skin
- on open wounds or damaged skin

Ask a doctor before use if you have redness over the affected area

When using this product

- avoid contact with eyes
- do not bandage tightly

Stop use and consult a doctor if

- skin redness or excessive skin irritation develops
- condition worsens or symptoms persist for more than 7 days
- symptoms clear up and occur again in a few days

Keep out of reach of children.

If swallowed, get medical help or contact a Poison Control Center right away.

Directions

Adults and children 12 years of age and older: Apply to affected area no more than 3-4 times daily.

Children under 12 years of age: Consult a doctor.

Other information

Store at room termperature. For Lot Number and Expiration Date, see bottom of the carton or crimp at end of tube.

Inactive ingredients C13-14 Isoparaffin,

Citrus Aurantium Dulcis (Orange) Oil,

Ethylhexylglycerin, Eucalyptus Globulus Oil,

Glyceryl Stearate, Laureth-7, Oxidized Corn

Oil, PEG-100 Stearate, Phenoxyethanol,

Polyacrylamide, Polysorbate-20, Water

PACKAGE LABEL

Dr. Pergolizzi

OxyRub

PRO

Pain Relief Cream

PROFESSIONAL STRENGTH

MUSCLE & JOINT

PAIN RELIEF

RAPIDLY

ABSORBED

DEEP

PENETRATING

Net Wt. 4 oz (114 g)

Distributed by

HEALTHY DIRECTIONS

6710A Rockledge Drive, Suite 500

Bethesda, MD 20817